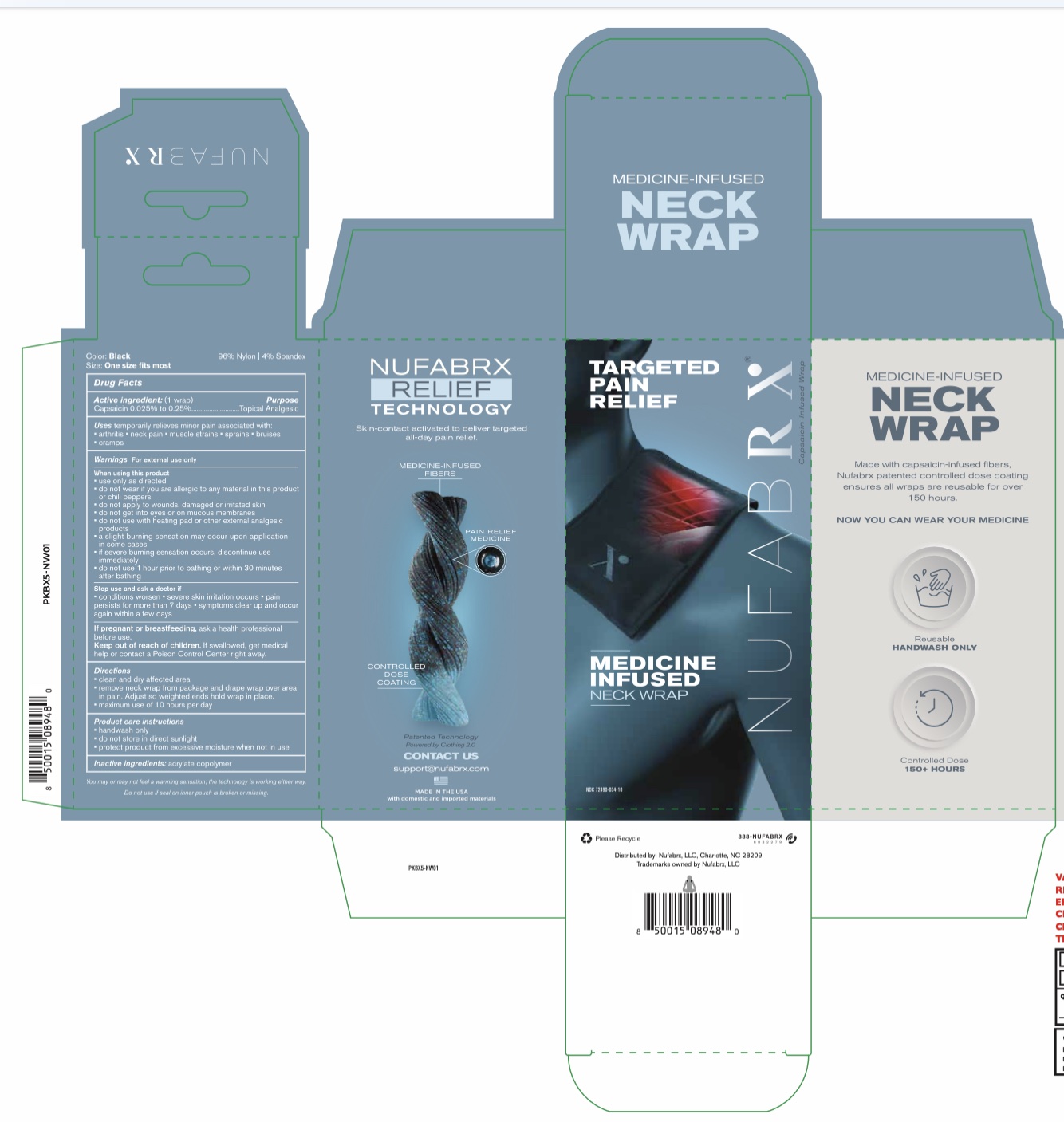 DRUG LABEL: Nufabrx Neck Wrap
NDC: 72490-034 | Form: CLOTH
Manufacturer: Nufabrx LLC
Category: otc | Type: HUMAN OTC DRUG LABEL
Date: 20251015

ACTIVE INGREDIENTS: CAPSAICIN 0.19 g/100 g
INACTIVE INGREDIENTS: BUTYL ACRYLATE/METHYL METHACRYLATE/METHACRYLIC ACID COPOLYMER (18000 MW)

72490-034 Nufabrx Neck Wrap

Active ingredient

Capsaicin (Nonivamide) 0.19%

Purpose

Topical Analgesic

Uses

For the temporary relief of minor aches and pains of muscles and joints associated with: simple backache, arthritis, strains, bruises and sprains.

Warnings

For external use only

Do not use

- If you are allergic to any ingredients of this product or chili peppers, contact a doctor before use (allergy alert)
- On wounds or damaged skin
- With, or at the same time as, other external analgesic products
- With a heating pad

When using this product

- You may experience a burning sensation which is normal and related to the way the product works (with regular use, this sensation generally diminishes)
- Do not use immediately before or after activities such as swimming, showering, sunbathing or intense exercise
- Use only as directed
- Avoid contact with eyes and mucous membranes or rashes

Stop use and ask doctor if

- Condition worsens, symptoms persist more than 7 days or clear up and occur again within a few days
- Rash, itching or excessive skin irritation develops

If pregnant or breastfeeding

Consult a healthcare professional before use

Keep out of reach of children

If swallowed, get medical help or contact a Poison Control Center right away

Directions

- Clean and dry affected area
- Remove sleeve from packaging and place on neck
- Maximum use of 10 hours per day
- Hand wash only
- Do not wear more than 6 days straight without doctor consent
- Wash hands after applying

Other information

Avoid storing product in direct sunlight. Protect product from excessive moisture.

Inactive ingredients

Acrylate copolymer